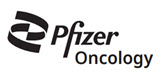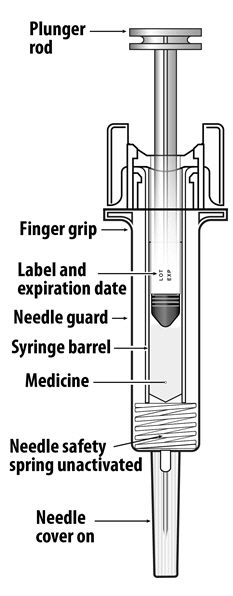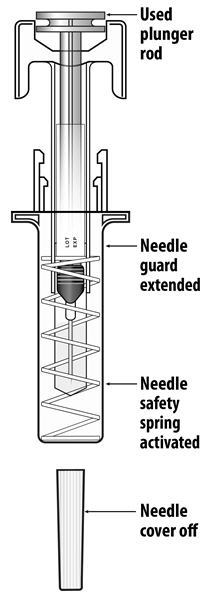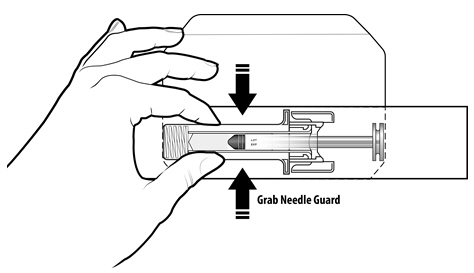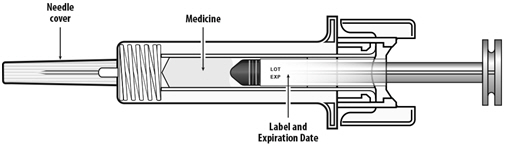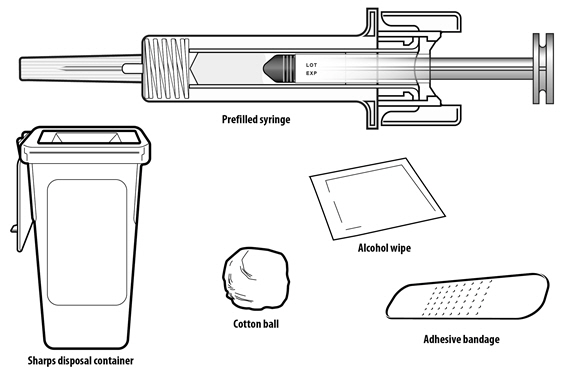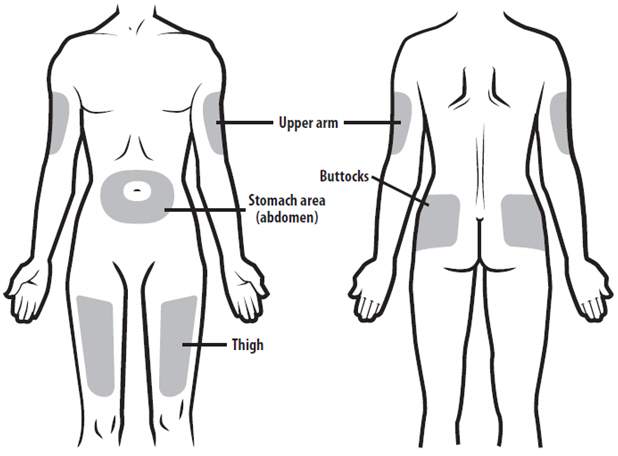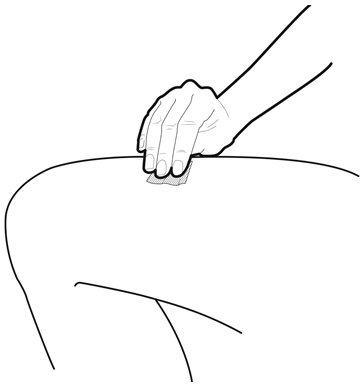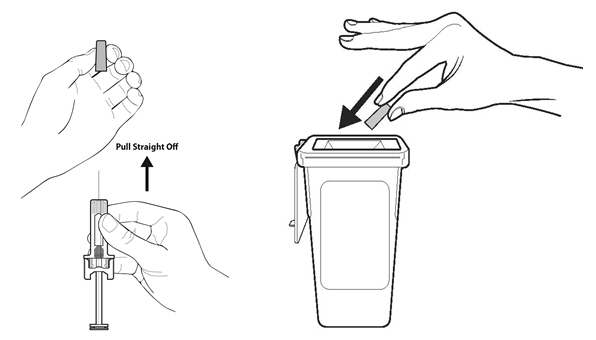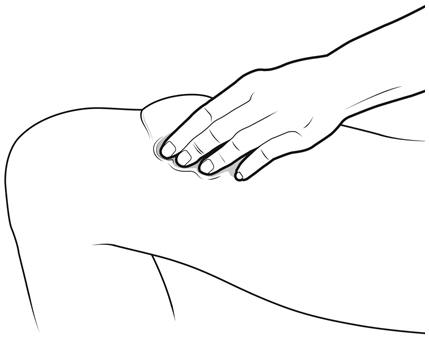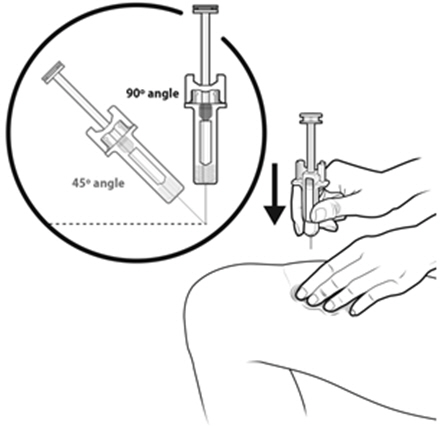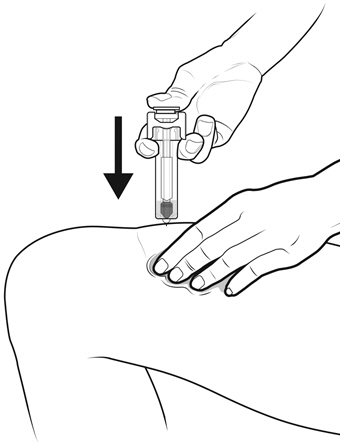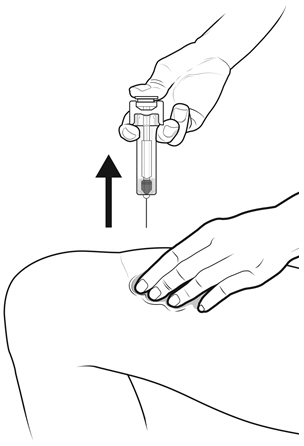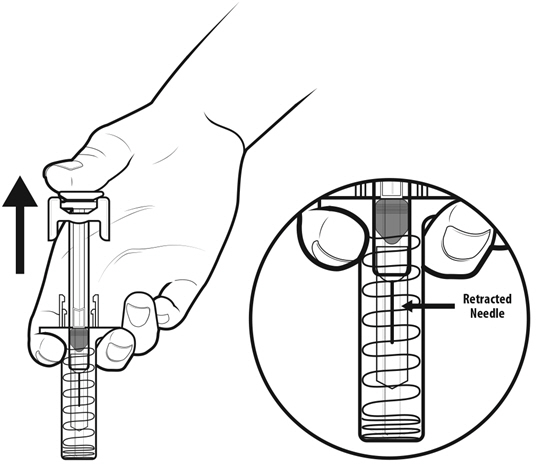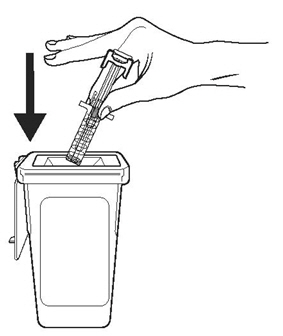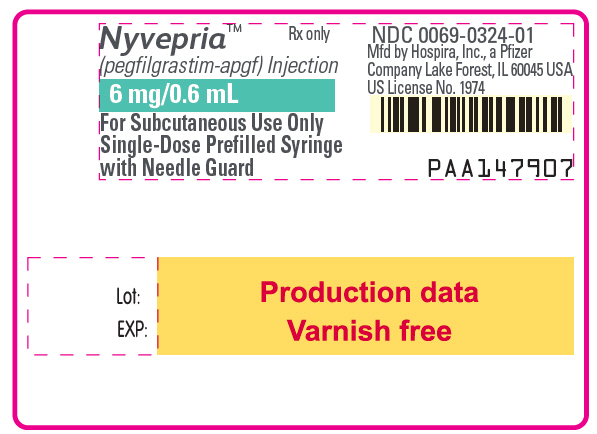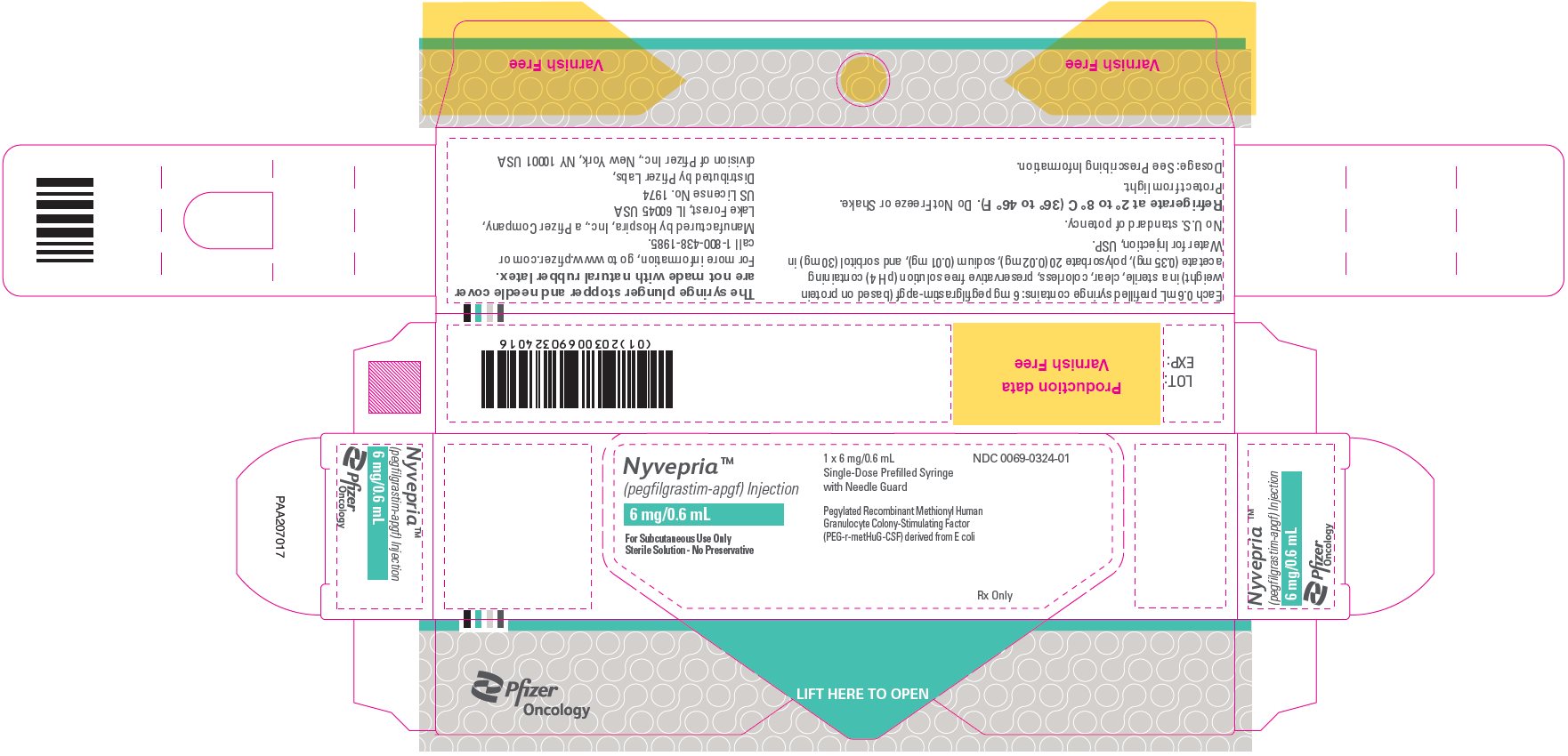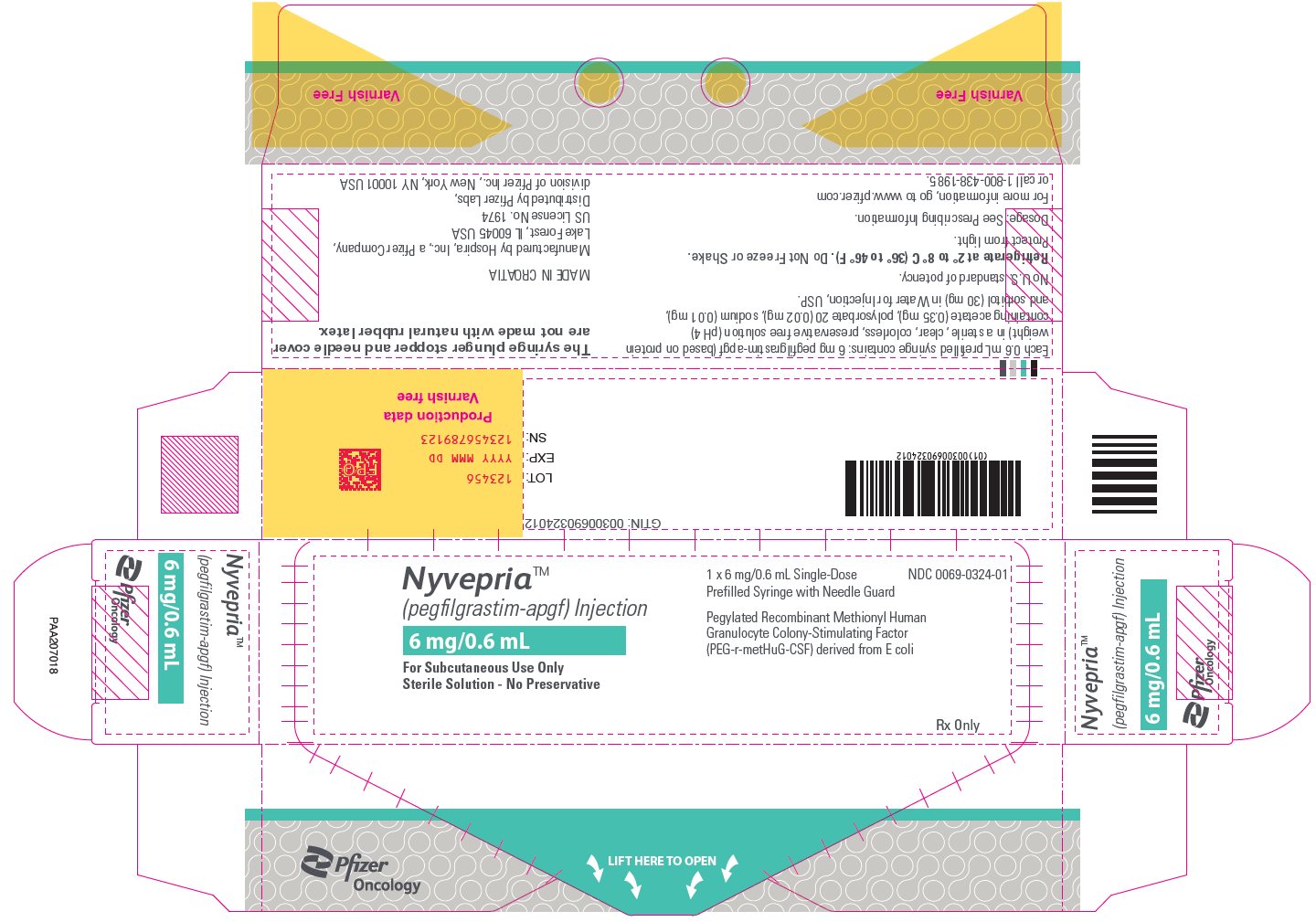 DRUG LABEL: NYVEPRIA
NDC: 0069-0324 | Form: INJECTION, SOLUTION
Manufacturer: Pfizer Laboratories Div Pfizer Inc
Category: prescription | Type: HUMAN PRESCRIPTION DRUG LABEL
Date: 20230629

ACTIVE INGREDIENTS: PEGFILGRASTIM 6 mg/0.6 mL
INACTIVE INGREDIENTS: ACETIC ACID; POLYSORBATE 20; SODIUM ACETATE; SORBITOL; WATER

HIGHLIGHTS OF PRESCRIBING INFORMATION

These highlights do not include all the information needed to use NYVEPRIA safely and effectively. See full prescribing information for NYVEPRIA.
NYVEPRIA™ (pegfilgrastim-apgf) injection, for subcutaneous use
Initial U.S. Approval: 2020

MICROBIOLOGY

NYVEPRIA (pegfilgrastim-apgf) is biosimilar* to NEULASTA (pegfilgrastim)

RECENT MAJOR CHANGES

Warnings and Precautions, Thrombocytopenia (5.7) | 04/2021
Warnings and Precautions, Myelodysplastic Syndrome (MDS) and Acute Myeloid Leukemia (AML) (5.10) | 04/2021

1 INDICATIONS AND USAGE

NYVEPRIA is a leukocyte growth factor indicated to decrease the incidence of infection, as manifested by febrile neutropenia, in patients with non-myeloid malignancies receiving myelosuppressive anti-cancer drugs associated with a clinically significant incidence of febrile neutropenia. (1)

Limitations of Use

NYVEPRIA is not indicated for the mobilization of peripheral blood progenitor cells for hematopoietic stem cell transplantation. (1)

2 DOSAGE AND ADMINISTRATION

Patients with cancer receiving myelosuppressive chemotherapy

- 6 mg administered subcutaneously once per chemotherapy cycle. (2.1)
- Do not administer between 14 days before and 24 hours after administration of cytotoxic chemotherapy. (2.1)
- Use weight based dosing for pediatric patients weighing less than 45 kg; refer to Table 1. (2.2)

3 DOSAGE FORMS AND STRENGTHS

Injection: 6 mg/0.6 mL solution in a single-dose prefilled syringe for manual use only. (3)

4 CONTRAINDICATIONS

Patients with a history of serious allergic reactions to human granulocyte colony-stimulating factors such as pegfilgrastim products or filgrastim products. (4)

5 WARNINGS AND PRECAUTIONS

- Fatal splenic rupture: Evaluate patients who report left upper abdominal or shoulder pain for an enlarged spleen or splenic rupture. (5.1)
- Acute respiratory distress syndrome (ARDS): Evaluate patients who develop fever, lung infiltrates, or respiratory distress. Discontinue NYVEPRIA in patients with ARDS. (5.2)
- Serious allergic reactions, including anaphylaxis: Permanently discontinue NYVEPRIA in patients with serious allergic reactions. (5.3)
- Fatal sickle cell crises: Discontinue NYVEPRIA if sickle cell crisis occurs. (5.4)
- Glomerulonephritis: Evaluate and consider dose-reduction or interruption of NYVEPRIA if causality is likely. (5.5)
- Thrombocytopenia: Monitor platelet counts. (5.7)
- Myelodysplastic Syndrome (MDS) and Acute Myeloid Leukemia (AML): Monitor patients with breast and lung cancer using NYVEPRIA in conjunction with chemotherapy and/or radiotherapy for signs and symptoms of MDS/AML. (5.10)

6 ADVERSE REACTIONS

Most common adverse reactions (≥5% difference in incidence compared to placebo) are bone pain and pain in extremity. (6.1)

To report SUSPECTED ADVERSE REACTIONS, contact Pfizer Inc. at 1-800-438-1985 or FDA at 1-800-FDA-1088 or www.fda.gov/medwatch.

*Biosimilar means that the biological product is approved based on data demonstrating that it is highly similar to an FDA-approved biological product, known as a reference product, and that there are no clinically meaningful differences between the biosimilar product and the reference product.
Biosimilarity of NYVEPRIA has been demonstrated for the condition(s) of use (e.g., indication(s), dosing regimen(s)), strength(s), dosage form(s), and route(s) of administration described in its Full Prescribing Information.

FULL PRESCRIBING INFORMATION

1 INDICATIONS AND USAGE

NYVEPRIA is indicated to decrease the incidence of infection, as manifested by febrile neutropenia, in patients with non-myeloid malignancies receiving myelosuppressive anti-cancer drugs associated with a clinically significant incidence of febrile neutropenia [see Clinical Studies (14)].

Limitations of Use

NYVEPRIA is not indicated for the mobilization of peripheral blood progenitor cells for hematopoietic stem cell transplantation.

2 DOSAGE AND ADMINISTRATION

2.1 Patients with Cancer Receiving Myelosuppressive Chemotherapy

The recommended dosage of NYVEPRIA is a single subcutaneous injection of 6 mg administered once per chemotherapy cycle. For dosing in pediatric patients weighing less than 45 kg, refer to Table 1. Do not administer NYVEPRIA between 14 days before and 24 hours after administration of cytotoxic chemotherapy.

2.2 Administration

NYVEPRIA is administered subcutaneously via a single-dose prefilled syringe for manual use.

Prior to use‚ remove the carton from the refrigerator and allow the NYVEPRIA prefilled syringe to reach room temperature for a minimum of 30 minutes. Discard any prefilled syringe left at room temperature for greater than 15 days.

Parenteral drug products should be inspected visually for particulate matter and discoloration prior to administration, whenever solution and container permit. NYVEPRIA is supplied as a clear and colorless solution. Do not administer NYVEPRIA if discoloration or particulates are observed.

The NYVEPRIA syringe plunger stopper and needle cover are not made with natural rubber latex.

Pediatric Patients Weighing Less than 45 kg

The NYVEPRIA prefilled syringe is not designed to allow for direct administration of doses less than 0.6 mL (6 mg). The syringe does not bear graduation marks, which are necessary to accurately measure doses of NYVEPRIA less than 0.6 mL (6 mg) for direct administration to patients. Thus, the direct administration to patients requiring dosing of less than 0.6 mL (6 mg) is not recommended due to the potential for dosing errors. Refer to Table 1.

Table 1. Dosing of NYVEPRIA for Pediatric Patients Weighing Less than 45 kg
Body Weight | NYVEPRIA Dose | Volume to Administer
Less than 10 kg [For pediatric patients weighing less than 10 kg, administer 0.1 mg/kg (0.01 mL/kg) of NYVEPRIA.] | See below | See below
10 – 20 kg | 1.5 mg | 0.15 mL
21 – 30 kg | 2.5 mg | 0.25 mL
31 – 44 kg | 4 mg | 0.4 mL

3 DOSAGE FORMS AND STRENGTHS

NYVEPRIA is a clear, colorless, preservative-free solution available as:

- Injection: 6 mg/0.6 mL in a single-dose prefilled syringe for manual use only.

4 CONTRAINDICATIONS

NYVEPRIA is contraindicated in patients with a history of serious allergic reactions to pegfilgrastim products or filgrastim products. Reactions have included anaphylaxis [see Warnings and Precautions (5.3)].

5 WARNINGS AND PRECAUTIONS

5.1 Splenic Rupture

Splenic rupture, including fatal cases, can occur following the administration of pegfilgrastim products. Evaluate for an enlarged spleen or splenic rupture in patients who report left upper abdominal or shoulder pain after receiving NYVEPRIA.

5.2 Acute Respiratory Distress Syndrome

Acute respiratory distress syndrome (ARDS) can occur in patients receiving pegfilgrastim products. Evaluate patients who develop fever and lung infiltrates or respiratory distress after receiving NYVEPRIA, for ARDS. Discontinue NYVEPRIA in patients with ARDS.

5.3 Serious Allergic Reactions

Serious allergic reactions, including anaphylaxis, can occur in patients receiving pegfilgrastim products. The majority of reported events occurred upon initial exposure. Allergic reactions, including anaphylaxis, can recur within days after the discontinuation of initial anti-allergic treatment. Permanently discontinue NYVEPRIA in patients with serious allergic reactions. Do not administer NYVEPRIA to patients with a history of serious allergic reactions to pegfilgrastim products or filgrastim products.

5.4 Use in Patients with Sickle Cell Disorders

Severe and sometimes fatal sickle cell crises can occur in patients with sickle cell disorders receiving pegfilgrastim products. Discontinue NYVEPRIA if sickle cell crisis occurs.

5.5 Glomerulonephritis

Glomerulonephritis has occurred in patients receiving pegfilgrastim products. The diagnoses were based upon azotemia, hematuria (microscopic and macroscopic), proteinuria, and renal biopsy. Generally, events of glomerulonephritis resolved after dose-reduction or discontinuation of pegfilgrastim products. If glomerulonephritis is suspected, evaluate for cause. If causality is likely, consider dose-reduction or interruption of NYVEPRIA.

5.6 Leukocytosis

White blood cell (WBC) counts of 100 × 10^9/L or greater have been observed in patients receiving pegfilgrastim products. Monitoring of complete blood count (CBC) during NYVEPRIA therapy is recommended.

5.7 Thrombocytopenia

Thrombocytopenia has been reported in patients receiving pegfilgrastim products. Monitor platelet counts.

5.8 Capillary Leak Syndrome

Capillary leak syndrome has been reported after G-CSF administration, including pegfilgrastim products, and is characterized by hypotension, hypoalbuminemia, edema and hemoconcentration. Episodes vary in frequency, severity and may be life-threatening if treatment is delayed. Patients who develop symptoms of capillary leak syndrome should be closely monitored and receive standard symptomatic treatment, which may include a need for intensive care.

5.9 Potential for Tumor Growth Stimulatory Effects on Malignant Cells

The granulocyte-colony stimulating factor (G-CSF) receptor through which pegfilgrastim products and filgrastim products act has been found on tumor cell lines. The possibility that pegfilgrastim products act as a growth factor for any tumor type, including myeloid malignancies and myelodysplasia, diseases for which pegfilgrastim products are not approved, cannot be excluded.

5.10 Myelodysplastic Syndrome (MDS) and Acute Myeloid Leukemia (AML) in Patients with Breast and Lung Cancer

MDS and AML have been associated with the use of pegfilgrastim products in conjunction with chemotherapy and/or radiotherapy in patients with breast and lung cancer. Monitor patients for signs and symptoms of MDS/AML in these settings.

5.11 Aortitis

Aortitis has been reported in patients receiving pegfilgrastim products. It may occur as early as the first week after start of therapy. Manifestations may include generalized signs and symptoms such as fever, abdominal pain, malaise, back pain, and increased inflammatory markers (e.g., c-reactive protein and white blood cell count). Consider aortitis in patients who develop these signs and symptoms without known etiology. Discontinue NYVEPRIA if aortitis is suspected.

5.12 Nuclear Imaging

Increased hematopoietic activity of the bone marrow in response to growth factor therapy has been associated with transient positive bone imaging changes. This should be considered when interpreting bone imaging results.

6 ADVERSE REACTIONS

The following clinically significant adverse reactions are discussed in greater detail in other sections of the labeling:

- Splenic Rupture [see Warnings and Precautions (5.1)]
- Acute Respiratory Distress Syndrome [see Warnings and Precautions (5.2)]
- Serious Allergic Reactions [see Warnings and Precautions (5.3)]
- Use in Patients with Sickle Cell Disorders [see Warnings and Precautions (5.4)]
- Glomerulonephritis [see Warnings and Precautions (5.5)]
- Leukocytosis [see Warnings and Precautions (5.6)]
- Thrombocytopenia [see Warnings and Precautions (5.7)]
- Capillary Leak Syndrome [see Warnings and Precautions (5.8)]
- Potential for Tumor Growth Stimulatory Effects on Malignant Cells [see Warnings and Precautions (5.9)]
- Myelodysplastic Syndrome [see Warnings and Precautions (5.10)]
- Acute Myeloid Leukemia [see Warnings and Precautions (5.10)]
- Aortitis [see Warnings and Precautions (5.11)]

6.1 Clinical Trials Experience

Because clinical trials are conducted under widely varying conditions, adverse reaction rates observed in the clinical trials of a drug cannot be directly compared to rates in the clinical trials of another drug and may not reflect the rates observed in practice.

Pegfilgrastim clinical trials safety data are based upon 932 patients receiving pegfilgrastim in seven randomized clinical trials. The population was 21 to 88 years of age and 92% female. The ethnicity was 75% Caucasian, 18% Hispanic, 5% Black, and 1% Asian. Patients with breast (n = 823), lung and thoracic tumors (n = 53) and lymphoma (n = 56) received pegfilgrastim after nonmyeloablative cytotoxic chemotherapy. Most patients received a single 100 mcg/kg (n = 259) or a single 6 mg (n = 546) dose per chemotherapy cycle over 4 cycles.

The following adverse reaction data in Table 2 are from a randomized, double-blind, placebo-controlled study in patients with metastatic or non-metastatic breast cancer receiving docetaxel 100 mg/m^2 every 21 days (Study 3). A total of 928 patients were randomized to receive either 6 mg pegfilgrastim (n = 467) or placebo (n = 461). The patients were 21 to 88 years of age and 99% female. The ethnicity was 66% Caucasian, 31% Hispanic, 2% Black, and <1% Asian, Native American, or other.

The most common adverse reactions occurring in ≥5% of patients and with a between-group difference of ≥5% higher in the pegfilgrastim arm in placebo-controlled clinical trials are bone pain and pain in extremity.

Table 2. Adverse Reactions with ≥5% Higher Incidence in Pegfilgrastim Patients Compared to Placebo in Study 3
Body System Adverse Reaction | Placebo (N = 461) | Pegfilgrastim 6 mg SC on Day 2 (N = 467)
Musculoskeletal and connective tissue disorders
Bone pain | 26% | 31%
Pain in extremity | 4% | 9%

Leukocytosis

In clinical studies, leukocytosis (WBC counts >100 × 10^9/L) was observed in less than 1% of 932 patients with non-myeloid malignancies receiving pegfilgrastim. No complications attributable to leukocytosis were reported in clinical studies.

6.2 Immunogenicity

As with all therapeutic proteins, there is potential for immunogenicity. The detection of antibody formation is highly dependent on the sensitivity and specificity of the assay. Additionally, the observed incidence of antibody (including neutralizing antibody) positivity in an assay may be influenced by several factors, including assay methodology, sample handling, timing of sample collection, concomitant medications, and underlying disease. For these reasons, comparison of the incidence of antibodies in the studies described below with the incidence of antibodies in other studies or to other pegfilgrastim products may be misleading.

Binding antibodies to pegfilgrastim were detected using a BIAcore assay. The approximate limit of detection for this assay is 500 ng/mL. Pre-existing binding antibodies were detected in approximately 6% (51/849) of patients with metastatic breast cancer. Four of 521 pegfilgrastim-treated subjects who were negative at baseline developed binding antibodies to pegfilgrastim following treatment. None of these 4 patients had evidence of neutralizing antibodies detected using a cell-based bioassay.

6.3 Postmarketing Experience

The following adverse reactions have been identified during post-approval use of pegfilgrastim products. Because these reactions are reported voluntarily from a population of uncertain size, it is not always possible to reliably estimate their frequency or establish a causal relationship to drug exposure.

- Splenic rupture and splenomegaly (enlarged spleen) [see Warnings and Precautions (5.1)]
- Acute respiratory distress syndrome (ARDS) [see Warnings and Precautions (5.2)]
- Allergic reactions/hypersensitivity, including anaphylaxis, skin rash, urticaria, generalized erythema, and flushing [see Warnings and Precautions (5.3)]
- Sickle cell crisis [see Warnings and Precautions (5.4)]
- Glomerulonephritis [see Warnings and Precautions (5.5)]
- Leukocytosis [see Warnings and Precautions (5.6)]
- Thrombocytopenia [see Warnings and Precautions (5.7)]
- Capillary Leak Syndrome [see Warnings and Precautions (5.8)]
- Injection site reactions
- Sweet's syndrome (acute febrile neutrophilic dermatosis), cutaneous vasculitis
- Myelodysplastic syndrome (MDS) and acute myeloid leukemia (AML) in patients with breast and lung cancer receiving chemotherapy and/or radiotherapy [see Warnings and Precautions (5.10)]
- Aortitis [see Warnings and Precautions (5.11)]
- Alveolar hemorrhage

8 USE IN SPECIFIC POPULATIONS

8.1 Pregnancy

Risk Summary

Although available data with NYVEPRIA or pegfilgrastim product use in pregnant women are insufficient to establish whether there is a drug associated risk of major birth defects, miscarriage, or adverse maternal or fetal outcomes, there are available data from published studies in pregnant women exposed to filgrastim products. These studies have not established an association of filgrastim product use during pregnancy with major birth defects, miscarriage, or adverse maternal or fetal outcomes.

In animal studies, no evidence of reproductive/developmental toxicity occurred in the offspring of pregnant rats that received cumulative doses of pegfilgrastim approximately 10 times the recommended human dose (based on body surface area). In pregnant rabbits, increased embryolethality and spontaneous abortions occurred at 4 times the maximum recommended human dose simultaneously with signs of maternal toxicity (see Data).

The estimated background risk of major birth defects and miscarriage for the indicated population is unknown. All pregnancies have a background risk of birth defect, loss, or other adverse outcomes. In the U.S. general population, the estimated background risk of major birth defects and miscarriage in clinically recognized pregnancies is 2 to 4% and 15 to 20%, respectively.

Data

Animal Data

Pregnant rabbits were dosed with pegfilgrastim subcutaneously every other day during the period of organogenesis. At cumulative doses ranging from the approximate human dose to approximately 4 times the recommended human dose (based on body surface area), the treated rabbits exhibited decreased maternal food consumption, maternal weight loss, as well as reduced fetal body weights and delayed ossification of the fetal skull; however, no structural anomalies were observed in the offspring from either study. Increased incidences of post-implantation losses and spontaneous abortions (more than half the pregnancies) were observed at cumulative doses approximately 4 times the recommended human dose, which were not seen when pregnant rabbits were exposed to the recommended human dose.

Three studies were conducted in pregnant rats dosed with pegfilgrastim at cumulative doses up to approximately 10 times the recommended human dose at the following stages of gestation: during the period of organogenesis, from mating through the first half of pregnancy, and from the first trimester through delivery and lactation. No evidence of fetal loss or structural malformations was observed in any study. Cumulative doses equivalent to approximately 3 and 10 times the recommended human dose resulted in transient evidence of wavy ribs in fetuses of treated mothers (detected at the end of gestation but no longer present in pups evaluated at the end of lactation).

8.2 Lactation

Risk Summary

There are no data on the presence of pegfilgrastim products in human milk, the effects on the breastfed child, or the effects on milk production. Other filgrastim products are secreted poorly into breast milk, and filgrastim products are not absorbed orally by neonates. The developmental and health benefits of breastfeeding should be considered along with the mother's clinical need for NYVEPRIA and any potential adverse effects on the breastfed child from NYVEPRIA or from the underlying maternal condition.

8.4 Pediatric Use

The safety and effectiveness of pegfilgrastim have been established in pediatric patients. No overall differences in safety were identified between adult and pediatric patients based on postmarketing surveillance and review of the scientific literature.

Use of pegfilgrastim in pediatric patients for chemotherapy-induced neutropenia is based on adequate and well-controlled studies in adults with additional pharmacokinetic and safety data in pediatric patients with sarcoma [see Clinical Pharmacology (12.3) and Clinical Studies (14)].

8.5 Geriatric Use

Of the 932 patients with cancer who received pegfilgrastim in clinical studies, 139 (15%) were aged 65 and over, and 18 (2%) were aged 75 and over. No overall differences in safety or effectiveness were observed between patients aged 65 and older and younger patients.

10 OVERDOSAGE

Overdosage of pegfilgrastim products may result in leukocytosis and bone pain. Events of edema, dyspnea, and pleural effusion have been reported in a single patient who administered pegfilgrastim on 8 consecutive days in error. In the event of overdose, the patient should be monitored for adverse reactions [see Adverse Reactions (6)].

11 DESCRIPTION

Pegfilgrastim-apgf is a covalent conjugate of recombinant methionyl human G-CSF and monomethoxypolyethylene glycol. Recombinant methionyl human G-CSF is a water-soluble 175 amino acid protein with a molecular weight of approximately 19 kilodaltons (kD). Recombinant methionyl human G-CSF is obtained from the bacterial fermentation of a strain of E. coli transformed with a genetically engineered plasmid containing the human G-CSF gene. To produce pegfilgrastim-apgf, a 20 kD monomethoxypolyethylene glycol molecule is covalently bound to the N-terminal methionyl residue of recombinant methionyl human G-CSF. The average molecular weight of pegfilgrastim-apgf is approximately 39 kD.

NYVEPRIA for manual subcutaneous injection is supplied in 0.6 mL prefilled syringes. The prefilled syringe does not bear graduation marks and is designed to deliver the entire contents of the syringe (6 mg/0.6 mL).

The delivered 0.6 mL dose from the prefilled syringe for manual subcutaneous injection contains 6 mg pegfilgrastim-apgf (based on protein weight) in a sterile, clear, colorless, preservative-free solution (pH 4.0) containing acetate (0.35 mg), polysorbate 20 (0.02 mg), sodium (0.01 mg), and sorbitol (30 mg) in Water for Injection, USP.

12 CLINICAL PHARMACOLOGY

12.1 Mechanism of Action

Pegfilgrastim products are colony-stimulating factors that act on hematopoietic cells by binding to specific cell surface receptors, thereby stimulating proliferation, differentiation, commitment, and end cell functional activation.

12.2 Pharmacodynamics

Animal data and clinical data in humans suggest a correlation between pegfilgrastim products' exposure and the duration of severe neutropenia as a predictor of efficacy. Selection of the dosing regimen of NYVEPRIA is based on reducing the duration of severe neutropenia.

12.3 Pharmacokinetics

The pharmacokinetics of pegfilgrastim was studied in 379 patients with cancer. The pharmacokinetics of pegfilgrastim was nonlinear, and clearance decreased with increases in dose. Neutrophil receptor binding is an important component of the clearance of pegfilgrastim, and serum clearance is directly related to the number of neutrophils. In addition to numbers of neutrophils, body weight appeared to be a factor. Patients with higher body weights experienced higher systemic exposure to pegfilgrastim after receiving a dose normalized for body weight. A large variability in the pharmacokinetics of pegfilgrastim was observed. The half-life of pegfilgrastim ranged from 15 to 80 hours after subcutaneous injection.

Specific Populations

No gender-related differences were observed in the pharmacokinetics of pegfilgrastim, and no differences were observed in the pharmacokinetics of geriatric patients (≥65 years of age) compared with younger patients (<65 years of age) [see Use in Specific Populations (8.5)].

Renal Impairment

In a study of 30 subjects with varying degrees of renal dysfunction, including end stage renal disease, renal dysfunction had no effect on the pharmacokinetics of pegfilgrastim.

Pediatric Patients with Cancer Receiving Myelosuppressive Chemotherapy

The pharmacokinetics and safety of pegfilgrastim were studied in 37 pediatric patients with sarcoma in Study 4 [see Clinical Studies (14)]. The mean (± standard deviation [SD]) systemic exposure (AUC0–inf) of pegfilgrastim after subcutaneous administration at 100 mcg/kg was 47.9 (± 22.5) mcg∙hr/mL in the youngest age group (0 to 5 years, n = 11), 22.0 (± 13.1) mcg∙hr/mL in the 6 to 11 years age group (n = 10), and 29.3 (± 23.2) mcg∙hr/mL in the 12 to 21 years age group (n = 13). The terminal elimination half-lives of the corresponding age groups were 30.1 (± 38.2) hours, 20.2 (± 11.3) hours, and 21.2 (± 16.0) hours, respectively.

13 NONCLINICAL TOXICOLOGY

13.1 Carcinogenesis, Mutagenesis, Impairment of Fertility

No carcinogenicity or mutagenesis studies have been performed with pegfilgrastim products.

Pegfilgrastim did not affect reproductive performance or fertility in male or female rats at cumulative weekly doses approximately 6 to 9 times higher than the recommended human dose (based on body surface area).

14 CLINICAL STUDIES

Pegfilgrastim was evaluated in three randomized, double-blind, controlled studies. Studies 1 and 2 were active-controlled studies that employed doxorubicin 60 mg/m^2 and docetaxel 75 mg/m^2 administered every 21 days for up to 4 cycles for the treatment of metastatic breast cancer. Study 1 investigated the utility of a fixed dose of pegfilgrastim. Study 2 employed a weight-adjusted dose. In the absence of growth factor support, similar chemotherapy regimens have been reported to result in a 100% incidence of severe neutropenia (ANC <0.5 × 10^9/L) with a mean duration of 5 to 7 days and a 30% to 40% incidence of febrile neutropenia. Based on the correlation between the duration of severe neutropenia and the incidence of febrile neutropenia found in studies with filgrastim, duration of severe neutropenia was chosen as the primary endpoint in both studies, and the efficacy of pegfilgrastim was demonstrated by establishing comparability to filgrastim-treated patients in the mean days of severe neutropenia.

In Study 1, 157 patients were randomized to receive a single subcutaneous injection of pegfilgrastim (6 mg) on day 2 of each chemotherapy cycle or daily subcutaneous filgrastim (5 mcg/kg/day) beginning on day 2 of each chemotherapy cycle. In Study 2, 310 patients were randomized to receive a single subcutaneous injection of pegfilgrastim (100 mcg/kg) on day 2 or daily subcutaneous filgrastim (5 mcg/kg/day) beginning on day 2 of each chemotherapy cycle.

Both studies met the major efficacy outcome measure of demonstrating that the mean days of severe neutropenia of pegfilgrastim-treated patients did not exceed that of filgrastim-treated patients by more than 1 day in cycle 1 of chemotherapy. The mean days of cycle 1 severe neutropenia in Study 1 were 1.8 days in the pegfilgrastim arm compared to 1.6 days in the filgrastim arm [difference in means 0.2 (95% CI -0.2, 0.6)] and in Study 2 were 1.7 days in the pegfilgrastim arm compared to 1.6 days in the filgrastim arm [difference in means 0.1 (95% CI -0.2, 0.4)].

A secondary endpoint in both studies was days of severe neutropenia in cycles 2 through 4 with results similar to those for cycle 1.

Study 3 was a randomized, double-blind, placebo-controlled study that employed docetaxel 100 mg/m^2 administered every 21 days for up to 4 cycles for the treatment of metastatic or non-metastatic breast cancer. In this study, 928 patients were randomized to receive a single subcutaneous injection of pegfilgrastim (6 mg) or placebo on day 2 of each chemotherapy cycle. Study 3 met the major trial outcome measure of demonstrating that the incidence of febrile neutropenia (defined as temperature ≥38.2°C and ANC ≤0.5 × 10^9/L) was lower for pegfilgrastim-treated patients as compared to placebo-treated patients (1% versus 17%, respectively, p < 0.001). The incidence of hospitalizations (1% versus 14%) and IV anti-infective use (2% versus 10%) for the treatment of febrile neutropenia was also lower in the pegfilgrastim-treated patients compared to the placebo-treated patients.

Study 4 was a multicenter, randomized, open-label study to evaluate the efficacy, safety, and pharmacokinetics [see Clinical Pharmacology (12.3)] of pegfilgrastim in pediatric and young adult patients with sarcoma. Patients with sarcoma receiving chemotherapy age 0 to 21 years were eligible. Patients were randomized to receive subcutaneous pegfilgrastim as a single dose of 100 mcg/kg (n = 37) or subcutaneous filgrastim at a dose 5 mcg/kg/day (n = 6) following myelosuppressive chemotherapy. Recovery of neutrophil counts was similar in the pegfilgrastim and filgrastim groups. The most common adverse reaction reported was bone pain.

16 HOW SUPPLIED/STORAGE AND HANDLING

NYVEPRIA (pegfilgrastim-apgf) injection is a clear, colorless solution supplied in a prefilled single-dose syringe for manual use containing 6 mg pegfilgrastim-apgf, supplied with a 27-gauge 1/2-inch needle and a BD UltraSafe Plus™ Passive Needle Guard.

The NYVEPRIA syringe plunger stopper and needle cover are not made with natural rubber latex.

NYVEPRIA is provided in a dispensing pack containing one sterile 6 mg/0.6 mL prefilled syringe (NDC 0069-0324-01).

NYVEPRIA prefilled syringe does not bear graduation marks and is intended only to deliver the entire contents of the syringe (6 mg/0.6 mL) for direct administration. Use of the prefilled syringe is not recommended for direct administration for pediatric patients weighing less than 45 kg who require doses that are less than the full contents of the syringe.

STORAGE AND HANDLING

Store refrigerated between 36°F to 46°F (2°C to 8°C) in the carton to protect from light. Do not shake. Discard syringes stored at room temperature for more than 15 days. Avoid freezing; if frozen, thaw in the refrigerator before administration. Discard syringe if frozen more than once.

17 PATIENT COUNSELING INFORMATION

Advise the patient to read the FDA-approved patient labeling (Patient Information and Instructions for Use).

Advise patients of the following risks and potential risks with NYVEPRIA:

- Splenic rupture and splenomegaly
- Acute Respiratory Distress Syndrome
- Serious allergic reactions
- Sickle cell crisis
- Glomerulonephritis
- Increased risk of Myelodysplastic Syndrome and/or Acute Myeloid Leukemia in patients with breast and lung cancer who receive pegfilgrastim products in conjunction with chemotherapy and/or radiation therapy
- Capillary Leak Syndrome
- Aortitis

Instruct patients who self-administer NYVEPRIA using the single-dose prefilled syringe of the:

- Importance of following the Instructions for Use.
- Dangers of reusing syringes.
- Importance of following local requirements for proper disposal of used syringes.

This product's labeling may have been updated. For the most recent prescribing information, please visit www.pfizer.com.

Manufactured by
Hospira, Inc., a Pfizer Company,
Lake Forest, IL 60045 USA
US License No. 1974

Distributed by Pfizer Labs, division of Pfizer Inc., New York, NY 10001 USA

BD UltraSafe Plus is a trademark of Becton Dickinson and Company.

LAB-1186-4.0

Patient Information
NYVEPRIA™ (Nigh-VEP ree-ah)
(pegfilgrastim-apgf)
injection
Single-Dose Prefilled Syringe

What is NYVEPRIA?
NYVEPRIA is a man-made form of granulocyte colony-stimulating factor (G-CSF). G-CSF is a substance produced by the body. It stimulates the growth of neutrophils, a type of white blood cell important in the body's fight against infection.

Do not take NYVEPRIA if you have had a serious allergic reaction to pegfilgrastim products or filgrastim products.

Before you receive NYVEPRIA, tell your healthcare provider about all of your medical conditions, including if you:

- have a sickle cell disorder.
- have kidney problems.
- are pregnant or plan to become pregnant. It is not known if NYVEPRIA will harm your unborn baby.
- are breastfeeding or plan to breastfeed. It is not known if NYVEPRIA passes into your breast milk.

Tell your healthcare provider about all of the medicines you take, including prescription and over-the-counter medicines, vitamins, and herbal supplements.

How will I receive NYVEPRIA?

- NYVEPRIA is given as an injection under your skin (subcutaneous injection) by a healthcare provider. If your healthcare provider decides that the subcutaneous injections can be given at home by you or your caregiver, follow the detailed "Instructions for Use" that comes with your NYVEPRIA for information on how to prepare and inject a dose of NYVEPRIA.
- You and your caregiver will be shown how to prepare and inject NYVEPRIA before you use it.
- You should not inject a dose of NYVEPRIA to children weighing less than 45 kg from a NYVEPRIA prefilled syringe. A dose less than 0.6 mL (6 mg) cannot be accurately measured using the NYVEPRIA prefilled syringe.
- If you are receiving NYVEPRIA because you are also receiving chemotherapy, the last dose of NYVEPRIA should be injected at least 14 days before and 24 hours after your dose of chemotherapy.
- If you miss a dose of NYVEPRIA, talk to your healthcare provider about when you should give your next dose.

What are possible side effects of NYVEPRIA?
NYVEPRIA may cause serious side effects, including:

- Spleen rupture. Your spleen may become enlarged and can rupture. A ruptured spleen can cause death. Call your healthcare provider right away if you have pain in the left upper stomach area or your left shoulder.
- A serious lung problem called Acute Respiratory Distress Syndrome (ARDS). Call your healthcare provider or get emergency help right away if you have shortness of breath with or without a fever, trouble breathing, or a fast rate of breathing.
- Serious allergic reactions. NYVEPRIA can cause serious allergic reactions. These reactions can cause a rash over your whole body, shortness of breath, wheezing, dizziness, swelling around your mouth or eyes, fast heart rate, and sweating. If you have any of these symptoms, stop using NYVEPRIA and call your healthcare provider or get emergency medical help right away.
- Sickle cell crises. You may have a serious sickle cell crisis, which could lead to death, if you have a sickle cell disorder and receive NYVEPRIA. Call your healthcare provider right away if you have symptoms of sickle cell crisis such as pain or difficulty breathing.
- Kidney injury (glomerulonephritis). NYVEPRIA can cause kidney injury. Call your healthcare provider right away if you develop any of the following symptoms:
  - swelling of your face or ankles
  - blood in your urine or dark colored urine
  - you urinate less than usual
- Increased white blood cell count (leukocytosis). Your healthcare provider will check your blood during treatment with NYVEPRIA.
- Decreased platelet count (thrombocytopenia). Your healthcare provider will check your blood during treatment with NYVEPRIA. Tell your healthcare provider if you have unusual bleeding or bruising during treatment with NYVEPRIA. This could be a sign of decreased platelet counts, which may reduce the ability of your blood to clot.
- Capillary Leak Syndrome. NYVEPRIA can cause fluid to leak from blood vessels into your body's tissues. This condition is called "Capillary Leak Syndrome" (CLS). CLS can quickly cause you to have symptoms that may become life-threatening. Get emergency medical help right away if you develop any of the following symptoms:
  - swelling or puffiness and are urinating less than usual
  - trouble breathing
  - swelling of your stomach area (abdomen) and feeling of fullness
  - dizziness or feeling faint
  - a general feeling of tiredness
- Myelodysplastic syndrome and acute myeloid leukemia. If you have breast cancer or lung cancer, when NYVEPRIA is used with chemotherapy and radiation therapy, or with radiation therapy alone, you may have an increased risk of developing a precancerous blood condition called myelodysplastic syndrome (MDS) or a blood cancer called acute myeloid leukemia (AML). Symptoms of MDS and AML may include tiredness, fever, and easy bruising or bleeding. Call your healthcare provider if you develop these symptoms during treatment with NYVEPRIA.
- Inflammation of the aorta (aortitis). Inflammation of the aorta (the large blood vessel which transports blood from the heart to the body) has been reported in patients who received pegfilgrastim products. Symptoms may include fever, abdominal pain, feeling tired, and back pain. Call your healthcare provider if you experience these symptoms.
The most common side effects of NYVEPRIA are pain in the bones, arms, and legs. These are not all the possible side effects of NYVEPRIA. Call your healthcare provider for medical advice about side effects. You may report side effects to FDA at 1-800-FDA-1088.

How should I store NYVEPRIA?

- Store NYVEPRIA in the refrigerator between 36°F to 46°F (2°C to 8°C).
- Do not freeze. If NYVEPRIA is accidentally frozen, allow the prefilled syringe to thaw in the refrigerator before injecting.
- Do not use a NYVEPRIA prefilled syringe that has been frozen more than 1 time. Use a new NYVEPRIA prefilled syringe.
- Keep the prefilled syringe in the original carton to protect from light or physical damage.
- Do not shake the prefilled syringe.
- Take NYVEPRIA out of the refrigerator 30 minutes before use and allow it to reach room temperature before preparing an injection.
- Throw away (dispose of) any NYVEPRIA that has been left at room temperature, 68°F to 77°F (20°C to 25°C), for more than 15 days.

Keep the NYVEPRIA prefilled syringe out of the reach of children.

General information about the safe and effective use of NYVEPRIA.
Medicines are sometimes prescribed for purposes other than those listed in a Patient Information leaflet. Do not use NYVEPRIA for a condition for which it was not prescribed. Do not give NYVEPRIA to other people, even if they have the same symptoms that you have. It may harm them. You can ask your pharmacist or healthcare provider for information about NYVEPRIA that is written for health professionals.

What are the ingredients in NYVEPRIA?
Active ingredient: pegfilgrastim-apgf.
Inactive ingredients: acetate, polysorbate 20, sodium, and sorbitol in water for injection.
Manufactured by Hospira, Inc., a Pfizer Company, Lake Forest, IL 60045 USA
US License No. 1974
Distributed by Pfizer Labs, division of Pfizer Inc., New York, NY 10001 USA

LAB-1187-4.0
For more information go to www.pfizer.com or call 1-800-438-1985.

This Patient Information has been approved by the U.S. Food and Drug Administration.

Revised: March 2023

Instructions for Use

NYVEPRIA (Nigh-VEP ree-ah)
(pegfilgrastim-apgf)
Injection, for subcutaneous use
Single-Dose Prefilled Syringe

Guide to parts

Before use

After use

Important: The needle is covered by the needle cover before use.

Important
Read the Patient Information for important information that you need to know about NYVEPRIA before using these Instructions for Use.
Before you use a NYVEPRIA prefilled syringe, read this important information.

Storing the prefilled syringe

- Store NYVEPRIA in the refrigerator between 36°F to 46°F (2°C to 8°C).
- Do not freeze. If NYVEPRIA is accidentally frozen, allow the prefilled syringe to thaw in the refrigerator before injecting.
- Do not use a NYVEPRIA prefilled syringe that has been frozen more than 1 time. Use a new NYVEPRIA prefilled syringe.
- Keep the prefilled syringe in the original carton to protect from light or physical damage.
  - Take the prefilled syringe out of the refrigerator 30 minutes before use and allow it to reach room temperature before preparing an injection.
  - Throw away (dispose of) any NYVEPRIA that has been left at room temperature, 68°F to 77°F (20°C to 25°C), for more than 15 days.
- Keep the NYVEPRIA prefilled syringe out of the reach of children.

Using the prefilled syringe

- It is important that you do not try to give the injection unless you or your caregiver has received training from your healthcare provider.
- Make sure the name NYVEPRIA appears on the carton and prefilled syringe label.
- Check the carton and prefilled syringe label to make sure the dose strength is 6 mg/0.6 mL.
- You should not inject a dose of NYVEPRIA to children weighing less than 45 kg from a NYVEPRIA prefilled syringe. A dose less than 0.6 mL (6 mg) cannot be accurately measured using the NYVEPRIA prefilled syringe.
- Do not use a prefilled syringe after the expiration date on the label.
- Do not shake the prefilled syringe.
  - Do not remove the needle cover from the prefilled syringe until you are ready to inject.
- Do not use the prefilled syringe if the carton is open or damaged.
- Do not use a prefilled syringe if it has been dropped on a hard surface. The prefilled syringe may be broken even if you cannot see the break. Use a new prefilled syringe.
- The prefilled syringe has a needle guard that automatically activates to cover the needle after the injection is given. Do not use a prefilled syringe if the needle guard has been activated. Use another prefilled syringe that has not been activated and is ready to use.

Call your healthcare provider if you have any questions.

Step 1: Prepare

A. Remove the prefilled syringe carton from the refrigerator.
Remove the inner carton containing the prefilled syringe from the outer carton by peeling away the cover. On a clean, well-lit surface, place the inner carton containing the prefilled syringe at room temperature for 30 minutes before you give an injection.

- Do not use the prefilled syringe if the inner carton containing the prefilled syringe is damaged.
- Do not try to warm the prefilled syringe by using a heat source such as hot water or microwave.
- Do not leave the prefilled syringe in direct sunlight.
- Do not shake the prefilled syringe.

Open the inner carton containing the prefilled syringe by peeling away the cover. Grab the needle guard to remove the prefilled syringe from the inner carton containing the prefilled syringe.For safety reasons:

- Do not grab the plunger rod.
- Do not grab the needle cover.

B. Inspect the medicine and prefilled syringe. Make sure the medicine in the prefilled syringe is clear and colorless.

- Do not use the prefilled syringe if:
  - The medicine is cloudy or discolored, or contains flakes or particles.
  - Any part appears cracked or broken.
  - The prefilled syringe has been dropped.
  - The needle cover is missing or not securely attached.
  - The expiration date printed on the label has passed.
In all cases, use a new prefilled syringe and call your healthcare provider.
  C. Gather all materials needed for the injection.
  Wash your hands thoroughly with soap and water.
  On a clean, well-lit work surface, place the:
- Prefilled syringe
- Alcohol wipe
- Cotton ball or gauze pad
- Adhesive bandage
- Sharps disposal container

Step 2: Get ready

D. Prepare and clean the injection site(s). You can use:
2. Thigh
3. Stomach area (abdomen), except for a 2-inch area right around the navel (belly button)
4. Upper outer area of the buttocks (only if someone else is giving you the injection)
5. Outer area of upper arm (only if someone else is giving you the injection)
Clean the injection site with an alcohol wipe. Let the skin dry.
7. Do not touch this area again before injecting.
8. If you want to use the same injection site, make sure it is not the same spot on the injection site you used for a previous injection.
9. Do not inject into areas where the skin is tender, bruised, red or hard. Avoid injecting into areas with scars or stretch marks.

E. Hold the prefilled syringe by the needle guard. Carefully pull the needle cover straight off and away from the body. Throw away the needle cover into the sharps disposal container. Do not recap.

- Do not remove the needle cover from the prefilled syringe until you are ready to inject.
- Do not twist or bend the needle cover.
- Do not hold the prefilled syringe by the plunger rod.
- Do not put the needle cover back onto the prefilled syringe.

Important: Throw the needle cover into the sharps disposal container.

Step 3: Subcutaneous (under the skin) injection

F. Pinch the injection site to create a firm surface. Important: Keep skin pinched while injecting.
G. Hold the pinch. Insert the needle into the skin at 45 to 90 degrees. H. Using slow and constant pressure, push the plunger rod down until it reaches the bottom.

Step 4: Finish

I. When the syringe is empty, keep the plunger rod fully pressed down while you carefully pull the needle straight out from the injection site and off your skin. J. Slowly release the plunger rod and allow the syringe needle guard to automatically cover the exposed needle. Do not recap the needle. Important: When you remove the syringe, if it looks like the medicine is still in the syringe barrel, this means you have not received a full dose. Call your healthcare provider right away.
K. Examine the injection site.
If there is blood, press a cotton ball or gauze pad on the injection site. Do not rub the injection site. Apply an adhesive bandage if needed.
L. Discard (throw away) the used prefilled syringe.

- Put the used prefilled syringe in a FDA-cleared sharps disposal container right away after use. Do not throw away (dispose of) the syringe in your household trash.
- If you do not have a FDA-cleared sharps disposal container, you may use a household container that is:
  - made of a heavy-duty plastic,
  - can be closed with a tight-fitting, puncture-resistant lid, without sharps being able to come out,
  - upright and stable during use,
  - leak-resistant, and
  - properly labeled to warn of hazardous waste inside the container.
- When your sharps disposal container is almost full, you will need to follow your community guidelines for the right way to dispose of your sharps disposal container. There may be state or local laws about how you should throw away used needles and syringes. For more information about safe sharps disposal, and for specific information about sharps disposal in the state that you live in, go to the FDA's website at: http://www.fda.gov/safesharpsdisposal.
- Do not reuse the prefilled syringe.
- Do not recycle the prefilled syringe or sharps disposal container or throw them in the household trash.
Important: Always keep the sharps disposal container out of the reach of children.
  This Instructions for Use has been approved by the U.S. Food and Drug Administration.
  Manufactured by
  Hospira, Inc., a Pfizer Company,
  Lake Forest, IL 60045 USA
  US License No. 1974
  Distributed by Pfizer Labs, division of Pfizer Inc., New York, NY 10001 USA

For more information go to www.pfizer.com or call 1-800-438-1985.
LAB-1188-3.0
Issued: March 2023

PRINCIPAL DISPLAY PANEL - 6 mg/0.6 mL Syringe Label

Nyvepria™
(pegfilgrastim-apgf) Injection

Rx only

6 mg/0.6 mL

For Subcutaneous Use Only
Single-Dose Prefilled Syringe
with Needle Guard

NDC 0069-0324-01
Mfd by Hospira, Inc., a Pfizer
Company Lake Forest, IL 60045 USA
US License No. 1974

PAA147907

PRINCIPAL DISPLAY PANEL - 6 mg/0.6 mL Syringe Inner Carton – PAA207017

Nyvepria™
(pegfilgrastim-apgf) Injection

6 mg/0.6 mL

For Subcutaneous Use Only
Sterile Solution - No Preservative

1 x 6 mg/0.6 mL
Single-Dose Prefilled Syringe
with Needle Guard

Pegylated Recombinant Methionyl Human
Granulocyte Colony-Stimulating Factor
(PEG-r-metHuG-CSF) derived from E coli

NDC 0069-0324-01

Rx Only

PRINCIPAL DISPLAY PANEL - 6 mg/0.6 mL Syringe Outer Carton – PAA207018

Nyvepria™
(pegfilgrastim-apgf) Injection

6 mg/0.6 mL

For Subcutaneous Use Only
Sterile Solution - No Preservative

1 x 6 mg/0.6 mL Single-Dose
Prefilled Syringe with Needle Guard

Pegylated Recombinant Methionyl Human
Granulocyte Colony-Stimulating Factor
(PEG-r-metHuG-CSF) derived from E coli

NDC 0069-0324-01

Rx Only